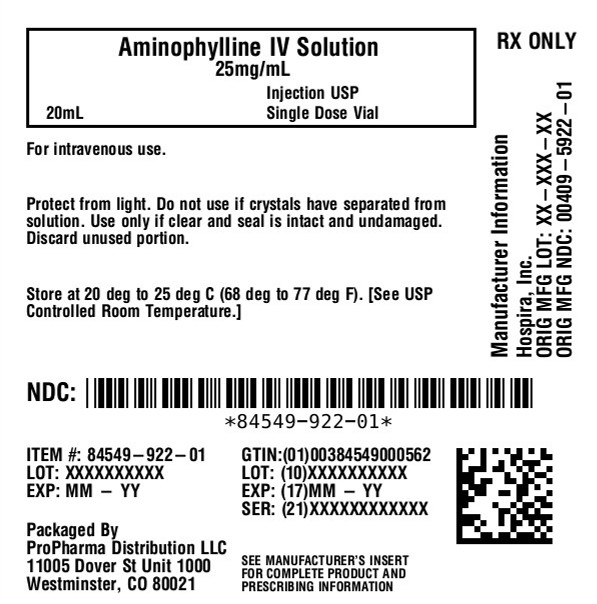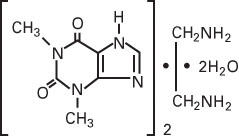 DRUG LABEL: Aminophylline
NDC: 84549-922 | Form: INJECTION, SOLUTION
Manufacturer: ProPharma Distribution
Category: prescription | Type: HUMAN PRESCRIPTION DRUG LABEL
Date: 20251218

ACTIVE INGREDIENTS: AMINOPHYLLINE DIHYDRATE 25 mg/1 mL
INACTIVE INGREDIENTS: ETHYLENEDIAMINE; WATER

Aminophylline
Injection, USP

25 mg/mL Aminophylline, Dihydrate
(Equivalent to 19.7 mg/mL of Anhydrous Theophylline)
Ampul
Fliptop Vial Rx only

DESCRIPTION

Aminophylline Injection, USP is a sterile, nonpyrogenic solution of aminophylline in water for injection. Aminophylline (dihydrate) is approximately 79% of anhydrous theophylline by weight. Aminophylline Injection is administered by slow intravenous injection or diluted and administered by intravenous infusion.

The solution contains no bacteriostat or antimicrobial agent and is intended for use only as a single-dose injection. When smaller doses are required the unused portion should be discarded.

Aminophylline is a 2:1 complex of theophylline and ethylenediamine. Theophylline is structurally classified as a methylxanthine. Aminophylline occurs as a white or slightly yellowish granule or powder, with a slight ammoniacal odor. Aminophylline has the chemical name 1H-Purine-2, 6-dione, 3,7-dihydro-1,3-dimethyl-, compound with 1,2-ethanediamine (2:1). The structural formula of aminophylline (dihydrate) is as follows:

The molecular formula of aminophylline dihydrate is C16H24N10O4• 2(H2O) with a molecular weight of 456.46.

Aminophylline Injection, USP contains aminophylline (calculated as the dihydrate) 25 mg/mL (equivalent to 19.7 mg/mL anhydrous theophylline) prepared with the aid of ethylenediamine. The solution may contain an excess of ethylenediamine for pH adjustment. pH is 8.8 (8.6 to 9.0). The osmolar concentration is 0.17 mOsmol/mL (calc.).

CLINICAL PHARMACOLOGY

Mechanism of Action:

Theophylline has two distinct actions in the airways of patients with reversible obstruction; smooth muscle relaxation (i.e., bronchodilation) and suppression of the response of the airways to stimuli (i.e., nonbronchodilator prophylactic effects). While the mechanisms of action of theophylline are not known with certainty, studies in animals suggest that bronchodilation is mediated by the inhibition of two isozymes of phosphodiesterase (PDE III and, to a lesser extent, PDE IV), while nonbronchodilator prophylactic actions are probably mediated through one or more different molecular mechanisms, that do not involve inhibition of PDE III or antagonism of adenosine receptors. Some of the adverse effects associated with theophylline appear to be mediated by inhibition of PDE III (e.g., hypotension, tachycardia, headache, and emesis) and adenosine receptor antagonism (e.g., alterations in cerebral blood flow).

Theophylline increases the force of contraction of diaphragmatic muscles. This action appears to be due to enhancement of calcium uptake through an adenosine-mediated channel.

Serum Concentration-Effect Relationship:

Bronchodilation occurs over the serum theophylline concentration range of 5 - 20 mcg/mL. Clinically important improvement in symptom control and pulmonary function has been found in most studies to require serum theophylline concentrations >10 mcg/mL. At serum theophylline concentrations >20 mcg/mL, both the frequency and severity of adverse reactions increase. In general, maintaining the average serum theophylline concentration between 10 and 15 mcg/mL will achieve most of the drug's potential therapeutic benefit while minimizing the risk of serious adverse events.

Pharmacokinetics:

Overview:The pharmacokinetics of theophylline vary widely among similar patients and cannot be predicted by age, sex, body weight or other demographic characteristics. In addition, certain concurrent illnesses and alterations in normal physiology (see Table I) and co-administration of other drugs (see Table II) can significantly alter the pharmacokinetic characteristics of theophylline. Within-subject variability in metabolism has also been reported in some studies, especially in acutely ill patients.

It is, therefore, recommended that serum theophylline concentrations be measured frequently in acutely ill patients receiving intravenous theophylline (e.g., at 24-hr. intervals). More frequent measurements should be made during the initiation of therapy and in the presence of any condition that may significantly alter theophylline clearance (see PRECAUTIONS, Effects on Laboratory Tests).

Table I. Mean and Range of Total Body Clearance and Half-Life of Theophylline Related to Age and Altered Physiological States¶
Population Characteristics; Age | Total Body Clearance*; Mean (Range)††; (mL/kg/min) | Half-Life; Mean (Range)††; (hr)
Premature neonates; postnatal age 3 - 15 days; postnatal age 25 - 57 days | 0.29 (0.09 - 0.49); 0.64 (0.04 - 1.2) | 30 (17 - 43); 20 (9.4 - 30.6)
Term infants; postnatal age 1 - 2 days; postnatal age 3 - 30 weeks | NR†; NR† | 25.7 (25 - 26.5); 11 (6 - 29)
Children; 1 - 4 years; 4 - 12 years; 13 - 15 years; 6 - 17 years | 1.7 (0.5 - 2.9); 1.6 (0.8 - 2.4); 0.9 (0.48 - 1.3); 1.4 (0.2 - 2.6) | 3.4 (1.2 - 5.6); NR†; NR†; 3.7 (1.5 - 5.9)
Adults (16 - 60 years); otherwise healthy; nonsmoking asthmatics | 0.65 (0.27 - 1.03) | 8.7 (6.1 - 12.8)
Elderly (>60 years); nonsmokers with normal cardiac,; liver, and renal function | 0.41 (0.21 - 0.61) | 9.8 (1.6 - 18)
Concurrent Illness Or Altered Physiological State
Acute pulmonary edema | 0.33** (0.07 - 2.45) | 19** (3.1 - 8.2)
COPD- >60 years, stable; nonsmoker >1 year | 0.54 (0.44 - 0.64) | 11 (9.4 - 12.6)
COPD with cor pulmonale | 0.48 (0.08 - 0.88) | NR†
Cystic fibrosis (14 - 28 years) | 1.25 (0.31 - 2.2) | 6 (1.8 - 10.2)
Fever associated with acute viral respiratory
illness (children 9 - 15 years) | NR† | 7 (1.0 - 13)
Liver disease – cirrhosis; acute hepatitis; cholestasis | 0.31** (0.1 - 0.7); 0.35 (0.25 - 0.45); 0.65 (0.25 - 1.45) | 32** (10 - 56); 19.2 (16.6 - 21.8); 14.4 (5.7 - 31.8)
Pregnancy – 1st trimester; 2nd trimester; 3rd trimester | NR†; NR†; NR† | 8.5 (3.1 - 13.9); 8.8 (3.8 - 13.8); 13 (8.4 - 17.6)
Sepsis with multi-organ failure | 0.47 (0.19 - 1.9) | 18.8 (6.3 - 24.1)
Thyroid disease – hypothyroid; hyperthyroid | 0.38 (0.13 - 0.57); 0.8 (0.68 - 0.97) | 11.6 (8.2 - 25); 4.5 (3.7 - 5.6)
¶ For various North American patient populations from literature reports. Different rates of elimination and consequent dosage requirements have been observed among other peoples.
* Clearance represents the volume of blood completely cleared of theophylline by the liver in one minute. Values listed were generally determined at serum theophylline concentrations, <20 mcg/mL; clearance may decrease and half-life may increase at higher serum concentrations due to nonlinear pharmacokinetics.
†† Reported range or estimated range (mean ± 2 SD) where actual range not reported.
† NR = not reported or not reported in a comparable format.
** Median

Note:In addition to the factors listed above, theophylline clearance is increased and half-life decreased by low carbohydrate/high protein diets, parenteral nutrition, and daily consumption of charcoal-broiled beef. A high carbohydrate/low protein diet can decrease the clearance and prolong the half-life of theophylline.

Distribution:Once theophylline enters the systemic circulation, about 40% is bound to plasma protein, primarily albumin. Unbound theophylline distributes throughout body water, but distributes poorly into body fat. The apparent volume of distribution of theophylline is approximately 0.45 L/kg (range 0.3 - 0.7 L/kg) based on ideal body weight. Theophylline passes freely across the placenta, into breast milk and into the cerebrospinal fluid (CSF). Saliva theophylline concentrations approximate unbound serum concentrations, but are not reliable for routine or therapeutic monitoring unless special techniques are used. An increase in the volume of distribution of theophylline, primarily due to reduction in plasma protein binding, occurs in premature neonates, patients with hepatic cirrhosis, uncorrected acidemia, the elderly and in women during the third trimester of pregnancy. In such cases, the patient may show signs of toxicity at total (bound + unbound) serum concentrations of theophylline in the therapeutic range (10 - 20 mcg/mL) due to elevated concentrations of the pharmacologically active unbound drug. Similarly, a patient with decreased theophylline binding may have a sub-therapeutic total drug concentration while the pharmacologically active unbound concentration is in the therapeutic range. If only total serum theophylline concentration is measured, this may lead to an unnecessary and potentially dangerous dose increase. In patients with reduced protein binding, measurement of unbound serum theophylline concentration provides a more reliable means of dosage adjustment than measurement of total serum theophylline concentration. Generally, concentrations of unbound theophylline should be maintained in the range of 6 - 12 mcg/mL.

Metabolism:In adults and children beyond one year of age, approximately 90% of the dose is metabolized in the liver. Biotransformation takes place through demethylation to 1-methylxanthine and 3-methylxanthine and hydroxylation to 1,3-dimethyluric acid. 1-methylxanthine is further hydroxylated, by xanthine oxidase, to 1-methyluric acid. About 6% of a theophylline dose is N-methylated to caffeine. Theophylline demethylation to 3-methylxanthine is catalyzed by cytochrome P-450 1A2, while cytochromes P-450 2E1 and P-450 3A3 catalyze the hydroxylation to 1,3-dimethyluric acid. Demethylation to 1-methylxanthine appears to be catalyzed either by cytochrome P-450 1A2 or a closely related cytochrome. In neonates, the N-demethylation pathway is absent while the function of the hydroxylation pathway is markedly deficient. The activity of these pathways slowly increases to maximal levels by one year of age.

Caffeine and 3-methylxanthine are the only theophylline metabolites with pharmacologic activity. 3-methylxanthine has approximately one tenth the pharmacologic activity of theophylline and serum concentrations in adults with normal renal function are <1 mcg/mL. In patients with end-stage renal disease, 3-methylxanthine may accumulate to concentrations that approximate the unmetabolized theophylline concentration. Caffeine concentrations are usually undetectable in adults regardless of renal function. In neonates, caffeine may accumulate to concentrations that approximate the unmetabolized theophylline concentration and thus, exert a pharmacologic effect.

Both the N-demethylation and hydroxylation pathways of theophylline biotransformation are capacity-limited. Due to the wide intersubject variability of the rate of theophylline metabolism, nonlinearity of elimination may begin in some patients at serum theophylline concentrations <10 mcg/mL. Since this nonlinearity results in more than proportional changes in serum theophylline concentrations with changes in dose, it is advisable to make increases or decreases in dose in small increments in order to achieve desired changes in serum theophylline concentrations (see DOSAGE AND ADMINISTRATION, Table VI). Accurate prediction of dose-dependency of theophylline metabolism in patients a prioriis not possible, but patients with very high initial clearance rates (i.e., low steady state serum theophylline concentrations at above average doses) have the greatest likelihood of experiencing large changes in serum theophylline concentration in response to dosage changes.

Excretion:In neonates, approximately 50% of the theophylline dose is excreted unchanged in the urine. Beyond the first three months of life, approximately 10% of the theophylline dose is excreted unchanged in the urine. The remainder is excreted in the urine mainly as 1,3-dimethyluric acid (35 - 40%), 1-methyluric acid (20 - 25%) and 3-methylxanthine (15 - 20%). Since little theophylline is excreted unchanged in the urine and since active metabolites of theophylline (i.e., caffeine, 3-methylxanthine) do not accumulate to clinically significant levels even in the face of end-stage renal disease, no dosage adjustment for renal insufficiency is necessary in adults and children >3 months of age. In contrast, the large fraction of the theophylline dose excreted in the urine as unchanged theophylline and caffeine in neonates requires careful attention to dose reduction and frequent monitoring of serum theophylline concentrations in neonates with reduced renal function (see WARNINGS).

Serum Concentrations at Steady State:In a patient who has received no theophylline in the previous 24 hours, a loading dose of intravenous theophylline of 4.6 mg/kg (5.7 mg/kg as aminophylline), calculated on the basis of ideal body weight and administered over 30 minutes, on average, will produce a maximum post-distribution serum concentration of 10 mcg/mL with a range of 6-16 mcg/mL. In non-smoking adults, initiation of a constant intravenous theophylline infusion of 0.4 mg/kg/hr (0.5 mg/kg/hr as aminophylline) at the completion of the loading dose, on average, will result in a steady-state concentration of 10 mcg/mL with a range of 7-26 mcg/mL. The mean and range of steady-state serum concentrations are similar when the average child (age 1 to 9 years) is given a loading dose of 4.6 mg/kg theophylline (5.7 mg/kg as aminophylline) followed by a constant intravenous infusion of 0.8 mg/kg/hr (1.0 mg/kg/hr as aminophylline) (see DOSAGE AND ADMINISTRATION).

Special Populations (see Table Ifor mean clearance and half-life values)

Geriatric:The clearance of theophylline is decreased by an average of 30% in healthy elderly adults (>60 yrs.) compared to healthy young adults. Careful attention to dose reduction and frequent monitoring of serum theophylline concentrations are required in elderly patients (see WARNINGS).

Pediatrics:The clearance of theophylline is very low in neonates (see WARNINGS). Theophylline clearance reaches maximal values by one year of age, remains relatively constant until about 9 years of age and then slowly decreases by approximately 50% to adult values at about age 16. Renal excretion of unchanged theophylline in neonates amounts to about 50% of the dose, compared to about 10% in children older than three months and in adults. Careful attention to dosage selection and monitoring of serum theophylline concentrations are required in children (see WARNINGSand DOSAGE AND ADMINISTRATION).

Gender:Gender differences in theophylline clearance are relatively small and unlikely to be of clinical significance. Significant reduction in theophylline clearance, however, has been reported in women on the 20th day of the menstrual cycle and during the third trimester of pregnancy.

Race:Pharmacokinetic differences in theophylline clearance due to race have not been studied.

Renal Insufficiency:Only a small fraction, e.g., about 10%, of the administered theophylline dose is excreted unchanged in the urine of children greater than three months of age and adults. Since little theophylline is excreted unchanged in the urine and since active metabolites of theophylline (i.e., caffeine, 3-methylxanthine) do not accumulate to clinically significant levels even in the face of end-stage renal disease, no dosage adjustment for renal insufficiency is necessary in adults and children >3 months of age. In contrast, approximately 50% of the administered theophylline dose is excreted unchanged in the urine in neonates. Careful attention to dose reduction and frequent monitoring of serum theophylline concentrations are required in neonates with decreased renal function (see WARNINGS).

Hepatic Insufficiency:Theophylline clearance is decreased by 50% or more in patients with hepatic insufficiency (e.g., cirrhosis, acute hepatitis, cholestasis). Careful attention to dose reduction and frequent monitoring of serum theophylline concentrations are required in patients with reduced hepatic function (see WARNINGS).

Congestive Heart Failure (CHF):Theophylline clearance is decreased by 50% or more in patients with CHF. The extent of reduction in theophylline clearance in patients with CHF appears to be directly correlated to the severity of the cardiac disease. Since theophylline clearance is independent of liver blood flow, the reduction in clearance appears to be due to impaired hepatocyte function rather than reduced perfusion. Careful attention to dose reduction and frequent monitoring of serum theophylline concentrations are required in patients with CHF (see WARNINGS).

Smokers:Tobacco and marijuana smoking appears to increase the clearance of theophylline by induction of metabolic pathways. Theophylline clearance has been shown to increase by approximately 50% in young adult tobacco smokers and by approximately 80% in elderly tobacco smokers compared to nonsmoking subjects. Passive smoke exposure has also been shown to increase theophylline clearance by up to 50%. Abstinence from tobacco smoking for one week causes a reduction of approximately 40% in theophylline clearance. Careful attention to dose reduction and frequent monitoring of serum theophylline concentrations are required in patients who stop smoking (see WARNINGS). Use of nicotine gum has been shown to have no effect on theophylline clearance.

Fever:Fever, regardless of its underlying cause, can decrease the clearance of theophylline. The magnitude and duration of the fever appear to be directly correlated to the degree of decrease of theophylline clearance. Precise data are lacking, but a temperature of 39°C (102°F) for at least 24 hours is probably required to produce a clinically significant increase in serum theophylline concentrations. Careful attention to dose reduction and frequent monitoring of serum theophylline concentrations are required in patients with sustained fever (see WARNINGS).

Miscellaneous:Other factors associated with decreased theophylline clearance include the third trimester of pregnancy, sepsis with multiple organ failure, and hypothyroidism. Careful attention to dose reduction and frequent monitoring of serum theophylline concentrations are required in patients with any of these conditions (see WARNINGS). Other factors associated with increased theophylline clearance include hyperthyroidism and cystic fibrosis.

Clinical Studies:

Inhaled beta-2 selective agonists and systemically administered corticosteroids are the treatments of first choice for management of acute exacerbations of asthma. The results of controlled clinical trials on the efficacy of adding intravenous theophylline to inhaled beta-2 selective agonists and systemically administered corticosteroids in the management of acute exacerbations of asthma have been conflicting. Most studies in patients treated for acute asthma exacerbations in an emergency department have shown that addition of intravenous theophylline does not produce greater bronchodilation and increases the risk of adverse effects. In contrast, other studies have shown that addition of intravenous theophylline is beneficial in the treatment of acute asthma exacerbations in patients requiring hospitalization, particularly in patients who are not responding adequately to inhaled beta-2 selective agonists.

In patients with chronic obstructive pulmonary disease (COPD), clinical studies have shown that theophylline decreases dyspnea, air trapping, the work of breathing, and improves contractility of diaphragmatic muscles with little or no improvement in pulmonary function measurements.

INDICATIONS AND USAGE

Intravenous theophylline is indicated as an adjunct to inhaled beta-2 selective agonists and systemically administered corticosteroids for the treatment of acute exacerbations of the symptoms and reversible airflow obstruction associated with asthma and other chronic lung diseases, e.g., emphysema and chronic bronchitis.

CONTRAINDICATIONS

Aminophylline is contraindicated in patients with a history of hypersensitivity to theophylline or other components in the product including ethylenediamine.

WARNINGS

Concurrent Illness:

Theophylline should be used with extreme caution in patients with the following clinical conditions due to the increased risk of exacerbation of the concurrent condition:

Active peptic ulcer disease
Seizure disorders
Cardiac arrhythmias (not including bradyarrhythmias)

Conditions That Reduce Theophylline Clearance:

There are several readily identifiable causes of reduced theophylline clearance. If the infusion rate is not appropriately reduced in the presence of these risk factors, severe and potentially fatal theophylline toxicity can occur.Careful consideration must be given to the benefits and risks of theophylline use and the need for more intensive monitoring of serum theophylline concentrations in patients with the following risk factors:

Age
Neonates (term and premature)
Children <1 year
Elderly (>60 years)

Concurrent Diseases
Acute pulmonary edema
Congestive heart failure
Cor pulmonale
Fever; ≥102° for 24 hours or more; or lesser temperature
elevations for longer periods
Hypothyroidism
Liver disease; cirrhosis, acute hepatitis
Reduced renal function in infants <3 months of age
Sepsis with multi-organ failure
Shock

Cessation of Smoking

Drug Interactions

Adding a drug that inhibits theophylline metabolism (e.g., cimetidine, erythromycin, tacrine) or stopping a concurrently administered drug that enhances theophylline metabolism (e.g., carbamazepine, rifampin) (see PRECAUTIONS, Drug Interactions, Table II).

When Signs or Symptoms of Theophylline Toxicity Are Present:

Whenever a patient receiving theophylline develops nausea or vomiting, particularly repetitive vomiting, or other signs or symptoms consistent with theophylline toxicity (even if another cause may be suspected), the intravenous infusion should be stopped and a serum theophylline concentration measured immediately.

Dosage Increases

Increases in the dose of intravenous theophylline should not be made in response to an acute exacerbation of symptoms unless the steady-state serum theophylline concentration is <10 mcg/mL.

As the rate of theophylline clearance may be dose-dependent (i.e., steady-state serum concentrations may increase disproportionately to the increase in dose), an increase in dose based upon a sub-therapeutic serum concentration measurement should be conservative. In general, limiting infusion rate increases to about 25% of the previous infusion rate will reduce the risk of unintended excessive increases in serum theophylline concentration (see DOSAGE AND ADMINISTRATION, TABLE VI).

PRECAUTIONS

General

Careful consideration of the various interacting drugs and physiologic conditions that can alter theophylline clearance and require dosage adjustment should occur prior to initiation of theophylline therapy and prior to increases in theophylline dose (see WARNINGS).

Monitoring Serum Theophylline Concentrations:

Serum theophylline concentration measurements are readily available and should be used to determine whether the dosage is appropriate. Specifically, the serum theophylline concentration should be measured as follows:

1. Before making a dose increase to determine whether the serum concentration is sub-therapeutic in a patient who continues to be symptomatic.
2. Whenever signs or symptoms of theophylline toxicity are present.
3. Whenever there is a new illness, worsening of an existing concurrent illness or a change in the patient's treatment regimen that may alter theophylline clearance (e.g., fever >102°F sustained for ≥24 hours, hepatitis, or drugs listed in Table II are added or discontinued).

In patients who have received no theophylline in the previous 24 hours, a serum concentration should be measured 30 minutes after completion of the intravenous loading dose to determine whether the serum concentration is <10 mcg/mL indicating the need for an additional loading dose or >20 mcg/mL indicating the need to delay starting the constant intravenous infusion. Once the infusion is begun, a second measurement should be obtained after one expected half-life (e.g., approximately 4 hours in children 1 to 9 years and 8 hours in non-smoking adults; see Table Ifor the expected half-life in additional patient populations). The second measurement should be compared to the first to determine the direction in which the serum concentration has changed. The infusion rate can then be adjusted before steady state is reached in an attempt to prevent an excessive or sub-therapeutic theophylline concentration from being achieved.

If a patient has received theophylline in the previous 24 hours, the serum concentration should be measured before administering an intravenous loading dose to make sure that it is safe to do so. If a loading dose is not indicated (i.e., the serum theophylline concentration is ≥10 mcg/mL), a second measurement should be obtained as above at the appropriate time after starting the intravenous infusion. If, on the other hand, a loading dose is indicated (see DOSAGE AND ADMINISTRATIONfor guidance on selection of the appropriate loading dose), a second blood sample should be obtained after the loading dose and a third sample should be obtained one expected half-life after starting the constant infusion to determine the direction in which the serum concentration has changed.

Once the above procedures related to initiation of intravenous theophylline infusion have been completed, subsequent serum samples for determination of theophylline concentration should be obtained at 24-hour intervals for the duration of the infusion. The theophylline infusion rate should be increased or decreased as appropriate based on the serum theophylline levels.

When signs or symptoms of theophylline toxicity are present, the intravenous infusion should be stopped and a serum sample for theophylline concentration should be obtained as soon as possible, analyzed immediately, and the result reported to the clinician without delay. In patients in whom decreased serum protein binding is suspected (e.g., cirrhosis, women during the third trimester of pregnancy), the concentration of unbound theophylline should be measured and the dosage adjusted to achieve an unbound concentration of 6-12 mcg/mL.

Saliva concentrations of theophylline cannot be used reliably to adjust dosage without special techniques.

Effects on Laboratory Tests:

As a result of its pharmacological effects, theophylline at serum concentrations within the 10 - 20 mcg/mL range modestly increases plasma glucose (from a mean of 88 mg% to 98 mg%), uric acid (from a mean of 4 mg/dl to 6 mg/dl), free fatty acids (from a mean of 451 µEq/L to 800 µEq/L), total cholesterol (from a mean of 140 vs 160 mg/dl), HDL (from a mean of 36 to 50 mg/dl), HDL/LDL ratio (from a mean of 0.5 to 0.7), and urinary free cortisol excretion (from a mean of 44 to 63 mcg/24 hr). Theophylline at serum concentrations within the 10 - 20 mcg/mL range may also transiently decrease serum concentrations of triiodothyronine (144 before, 131 after one week and 142 ng/dl after 4 weeks of theophylline). The clinical importance of these changes should be weighed against the potential therapeutic benefit of theophylline in individual patients.

Drug Interactions:

Theophylline interacts with a wide variety of drugs. The interaction may be pharmacodynamic, i.e., alterations in the therapeutic response to theophylline or another drug or occurrence of adverse effects without a change in serum theophylline concentration. More frequently, however, the interaction is pharmacokinetic, i.e., the rate of theophylline clearance is altered by another drug resulting in increased or decreased serum theophylline concentrations. Theophylline only rarely alters the pharmacokinetics of other drugs.

The drugs listed in Table II have the potential to produce clinically significant pharmacodynamic or pharmacokinetic interactions with theophylline. The information in the "Effect" column of Table IIassumes that the interacting drug is being added to a steady-state theophylline regimen. If theophylline is being initiated in a patient who is already taking a drug that inhibits theophylline clearance (e.g., cimetidine, erythromycin), the dose of theophylline required to achieve a therapeutic serum theophylline concentration will be smaller. Conversely, if theophylline is being initiated in a patient who is already taking a drug that enhances theophylline clearance (e.g., rifampin), the dose of theophylline required to achieve a therapeutic serum theophylline concentration will be larger. Discontinuation of a concomitant drug that increases theophylline clearance will result in accumulation of theophylline to potentially toxic levels, unless the theophylline dose is appropriately reduced. Discontinuation of a concomitant drug that inhibits theophylline clearance will result in decreased serum theophylline concentrations, unless the theophylline dose is appropriately increased.

The drugs listed in Table IIIhave either been documented not to interact with theophylline or do not produce a clinically significant interaction (i.e., <15% change in theophylline clearance).

The listing of drugs in Tables IIand IIIare current as of September 1, 1995. New interactions are continuously being reported for theophylline, especially with new chemical entities. The clinician should not assume that a drug does not interact with theophylline if it is not listed in Table II.Before addition of a newly available drug in a patient receiving theophylline, the package insert of the new drug and/or the medical literature should be consulted to determine if an interaction between the new drug and theophylline has been reported.

Table II. Clinically Significant Drug Interactions With Theophylline*
Drug | Type Of Interaction | Effect**
Adenosine | Theophylline blocks adenosine receptors. | Higher doses of adenosine may be required to achieve desired effect.
Alcohol | A single large dose of alcohol (3 mL/kg of whiskey) decreases theophylline clearance for up to 24 hours. | 30% increase
Allopurinol | Decreases theophylline clearance at allopurinol doses ≥600 mg/day. | 25% increase
Aminoglutethimide | Increases theophylline clearance by induction of microsomal enzyme activity. | 25% decrease
Carbamazepine | Similar to aminoglutethimide. | 30% decrease
Cimetidine | Decreases theophylline clearance by inhibiting cytochrome P450 1A2. | 70% increase
Ciprofloxacin | Similar to cimetidine. | 40% increase
Clarithromycin | Similar to erythromycin. | 25% increase
Diazepam | Benzodiazepines increase CNS concentrations of adenosine, a potent CNS depressant, while theophylline blocks adenosine receptors. | Larger diazepam doses may be required to produce desired level of sedation. Discontinuation of theophylline without reduction of diazepam dose may result in respiratory depression.
Disulfiram | Decreases theophylline clearance by inhibiting hydroxylation and demethylation. | 50% increase
Enoxacin | Similar to cimetidine. | 300% increase
Ephedrine | Synergistic CNS effects. | Increased frequency of nausea, nervousness, and insomnia.
Erythromycin | Erythromycin metabolite decreases theophylline clearance by inhibiting; cytochrome P450 3A3. | 35% increase. Erythromycin steady-state serum concentrations decrease by a similar amount.
Estrogen | Estrogen containing oral contraceptives decrease theophylline clearance in a dose-dependent fashion.; The effect of progesterone on theophylline clearance is unknown. | 30% increase
Flurazepam | Similar to diazepam. | Similar to diazepam.
Fluvoxamine | Similar to cimetidine. | Similar to cimetidine.
Halothane | Halothane sensitizes the myocardium to catecholamines, theophylline increases release of endogenous catecholamines. | Increased risk of ventricular arrhythmias.
Interferon, human recombinant alpha-A | Decreases theophylline clearance. | 100% increase
Isoproterenol (I.V.) | Increases theophylline clearance. | 20% decrease
Ketamine | Pharmacologic | May lower theophylline seizure threshold.
Lithium | Theophylline increases renal lithium clearance. | Lithium dose required to achieve a therapeutic serum concentration increased an average of 60%.
Lorazepam | Similar to diazepam. | Similar to diazepam.
Methotrexate (MTX) | Decreases theophylline clearance. | 20% increase after low dose MTX, higher dose MTX may have a greater effect.
Mexiletine | Similar to disulfiram. | 80% increase
Midazolam | Similar to diazepam. | Similar to diazepam.
Moricizine | Increases theophylline clearance. | 25% decrease
Pancuronium | Theophylline may antagonize nondepolarizing neuromuscular blocking effects; possibly due to phosphodiesterase inhibition. | Larger dose of pancuronium may be required to achieve neuromuscular blockade.
Pentoxifylline | Decreases theophylline clearance. | 30% increase
Phenobarbital (PB) | Similar to aminoglutethimide. | 25% decrease after two weeks of concurrent Phenobarbital.
Phenytoin | Phenytoin increases theophylline clearance by increasing microsomal enzyme activity. Theophylline decreases phenytoin absorption. | Serum theophylline and phenytoin concentrations decrease about 40%.
Propafenone | Decreases theophylline clearance and pharmacologic interaction. | 40% increase. Beta-2 blocking effect may decrease efficacy of theophylline.
Propranolol | Similar to cimetidine and pharmacologic interaction. | 100% increase. Beta-2 blocking effect may decrease efficacy of theophylline.
Rifampin | Increases theophylline clearance by increasing cytochrome P450 1A2 and 3A3 activity. | 20 - 40% decrease
Sulfinpyrazone | Increases theophylline clearance by increasing demethylation and hydroxylation. Decreases renal clearance of theophylline. | 20% decrease
Tacrine | Similar to cimetidine, also increases renal clearance of theophylline. | 90% increase
Thiabendazole | Decreases theophylline clearance. | 190% increase
Ticlopidine | Decreases theophylline clearance. | 60% increase
Troleandomycin | Similar to erythromycin. | 33 - 100% increase depending on troleandomycin dose.
Verapamil | Similar to disulfiram. | 20% increase
* Refer to PRECAUTIONS, Drug Interactionsfor further information regarding table.
** Average effect on steady-state theophylline concentration or other clinical effect for pharmacologic interactions. Individual patients may experience larger changes in serum theophylline concentration than the value listed.

Table III. Drugs That Have Been Documented Not to Interact With Theophylline or Drugs That Produce No Clinically Significant Interaction With Theophylline [Refer to PRECAUTIONS, Drug Interactions for information regarding table.]

albuterol,

systemic and inhaled

amoxicillin

ampicillin,

with or without sulbactam

atenolol

azithromycin

caffeine,

dietary ingestion

cefaclor

co-trimoxazole

(trimethoprim and sulfamethoxazole)

diltiazem

dirithromycin

enflurane

famotidine

felodipine

finasteride

hydrocortisone

isoflurane

isoniazid

isradipine

influenza vaccine

ketoconazole

lomefloxacin

mebendazole

medroxyprogesterone

methylprednisolone

metronidazole

metoprolol

nadolol

nifedipine

nizatidine

norfloxacin

ofloxacin

omeprazole

prednisone, prednisolone

ranitidine

rifabutin

roxithromycin

sorbitol

(purgative doses do not inhibit

theophylline absorption)

sucralfate

terbutaline, systemic

terfenadine

tetracycline

tocainide

The Effect of Other Drugs on Theophylline Serum Concentration Measurements:

Most serum theophylline assays in clinical use are immunoassays which are specific for theophylline. Other xanthines such as caffeine, dyphylline, and pentoxifylline are not detected by these assays. Some drugs (e.g., cefazolin, cephalothin), however, may interfere with certain HPLC techniques. Caffeine and xanthine metabolites in neonates or patients with renal dysfunction may cause the reading from some dry reagent office methods to be higher than the actual serum theophylline concentration.

Carcinogenesis, Mutagenesis, and Impairment of Fertility:

Long term carcinogenicity studies have been carried out in mice (oral doses 30 - 150 mg/kg) and rats (oral doses 5 - 75 mg/kg). Results are pending.

Theophylline has been studied in Ames salmonella, in vivoand in vitrocytogenetics, micronucleus and Chinese hamster ovary test systems and has not been shown to be genotoxic.

In a 14 week continuous breeding study, theophylline, administered to mating pairs of B6C3F1mice at oral doses of 120, 270 and 500 mg/kg (approximately 1.0 - 3.0 times the human dose on a mg/m^2basis) impaired fertility, as evidenced by decreases in the number of live pups per litter, decreases in the mean number of litters per fertile pair, and increases in the gestation period at the high dose as well as decreases in the proportion of pups born alive at the mid and high dose. In 13 week toxicity studies, theophylline was administered to F344 rats and B6C3F1mice at oral doses of 40 - 300 mg/kg (approximately 2 times the human dose on a mg/m^2basis). At the high dose, systemic toxicity was observed in both species including decreases in testicular weight.

Pregnancy:

There are no adequate and well controlled studies in pregnant women. Additionally, there are no teratogenicity studies in nonrodents (e.g., rabbits). Theophylline was not shown to be teratogenic in CD-1 mice at oral doses up to 400 mg/kg, approximately 2.0 times the human dose on a mg/m^2basis or in CD-1 rats at oral doses up to 260 mg/kg, approximately 3.0 times the recommended human dose on a mg/m^2basis. At a dose of 220 mg/kg, embryotoxicity was observed in rats in the absence of maternal toxicity.

Nursing Mothers:

Theophylline is excreted into breast milk and may cause irritability or other signs of mild toxicity in nursing human infants. The concentration of theophylline in breast milk is about equivalent to the maternal serum concentration. An infant ingesting a liter of breast milk containing 10 - 20 mcg/mL of theophylline per day is likely to receive 10 - 20 mg of theophylline per day. Serious adverse effects in the infant are unlikely unless the mother has toxic serum theophylline concentrations.

Pediatric Use:

Theophylline is safe and effective for the approved indications in pediatric patients (see INDICATIONS AND USAGE). The constant infusion rate of intravenous theophylline must be selected with caution in pediatric patients since the rate of theophylline clearance is highly variable across the age range of neonates to adolescents (see CLINICAL PHARMACOLOGY, Table I, WARNINGS, and DOSAGE AND ADMINISTRATION, Table V). Due to the immaturity of theophylline metabolic pathways in pediatric patients under the age of one year, particular attention to dosage selection and frequent monitoring of serum theophylline concentrations are required when theophylline is prescribed to pediatric patients in this age group.

Geriatric Use:

Elderly patients are at significantly greater risk of experiencing serious toxicity from theophylline than younger patients due to pharmacokinetic and pharmacodynamic changes associated with aging. Theophylline clearance is reduced in patients greater than 60 years of age, resulting in increased serum theophylline concentrations in response to a given theophylline infusion rate. Protein binding may be decreased in the elderly resulting in a larger proportion of the total serum theophylline concentration in the pharmacologically active unbound form. Elderly patients also appear to be more sensitive to the toxic effects of theophylline after chronic overdosage than younger patients. For these reasons, the maximum infusion rate of theophylline in patients greater than 60 years of age ordinarily should not exceed 17 mg/hr (21 mg/hr as aminophylline) unless the patient continues to be symptomatic and the peak steady state serum theophylline concentration is <10 mcg/mL (see DOSAGE AND ADMINISTRATION). Theophylline infusion rates greater than 17 mg/hr (21 mg/hr as aminophylline) should be prescribed with caution in elderly patients.

ADVERSE REACTIONS

Adverse reactions associated with theophylline are generally mild when peak serum theophylline concentrations are <20 mcg/mL and mainly consist of transient caffeine-like adverse effects such as nausea, vomiting, headache, and insomnia. When peak serum theophylline concentrations exceed 20 mcg/mL, however, theophylline produces a wide range of adverse reactions including persistent vomiting, cardiac arrhythmias, and intractable seizures which can be lethal (see OVERDOSAGE).

Other adverse reactions that have been reported at serum theophylline concentrations <20 mcg/mL include diarrhea, irritability, restlessness, fine skeletal muscle tremors, and transient diuresis. In patients with hypoxia secondary to COPD, multifocal atrial tachycardia and flutter have been reported at serum theophylline concentrations ≥15 mcg/mL. There have been a few isolated reports of seizures at serum theophylline concentrations <20 mcg/mL in patients with an underlying neurological disease or in elderly patients. The occurrence of seizures in elderly patients with serum theophylline concentrations <20 mcg/mL may be secondary to decreased protein binding resulting in a larger proportion of the total serum theophylline concentration in the pharmacologically active unbound form. The clinical characteristics of the seizures reported in patients with serum theophylline concentrations <20 mcg/mL have generally been milder than seizures associated with excessive serum theophylline concentrations resulting from an overdose (i.e., they have generally been transient, often stopped without anticonvulsant therapy, and did not result in neurological residua).

Products containing aminophylline may rarely produce severe allergic reactions of the skin, including exfoliative dermatitis, after systemic administration in a patient who has been previously sensitized by topical application of a substance containing ethylenediamine. In such patients skin patch tests are positive for ethylenediamine, a component of aminophylline, and negative for theophylline. Pharmacists and other individuals who experience repeated skin exposure while physically handling aminophylline may develop a contact dermatitis due to the ethylenediamine component.

Table IV. Manifestations of Theophylline Toxicity* Percentage of Patients Reported With Sign or Symptom
 | Acute Overdose; (Large Single Ingestion) |  | Chronic Overdosage; (Multiple Excessive Doses)
Sign/Symptom | Study 1; (n=157) | Study 2; (n=14) | Study 1; (n=92) | Study 2; (n=102)
Asymptomatic | NR** | 0 | NR** | 6
Gastrointestinal
Vomiting | 73 | 93 | 30 | 61
Abdominal pain | NR** | 21 | NR** | 12
Diarrhea | NR** | 0 | NR** | 14
Hematemesis | NR** | 0 | NR** | 2
Metabolic/Other
Hypokalemia | 85 | 79 | 44 | 43
Hyperglycemia | 98 | NR** | 18 | NR**
Acid/base disturbance | 34 | 21 | 9 | 5
Rhabdomyolysis | NR** | 7 | NR** | 0
Cardiovascular
Sinus tachycardia | 100 | 86 | 100 | 62
Other supraventricular | 2 | 21 | 12 | 14
tachycardias
Ventricular premature beats | 3 | 21 | 10 | 19
Atrial fibrillation or flutter | 1 | NR** | 12 | NR**
Multifocal atrial tachycardia | 0 | NR** | 2 | NR**
Ventricular arrhythmias with | 7 | 14 | 40 | 0
hemodynamic instability
Hypotension/shock | NR** | 21 | NR** | 8
Neurologic
Nervousness | NR** | 64 | NR** | 21
Tremors | 38 | 29 | 16 | 14
Disorientation | NR** | 7 | NR** | 11
Seizures | 5 | 14 | 14 | 5
Death | 3 | 21 | 10 | 4
* These data are derived from two studies in patients with serum theophylline concentrations
>30 mcg/mL. In the first study (Study #1 – Shanon, Ann Intern Med 1993;119:1161-67), data were prospectively collected from 249 consecutive cases of theophylline toxicity referred to a regional poison center for consultation. In the second study (Study #2 – Sessler, Am J Med 1990; 88:567-76), data were retrospectively collected from 116 cases with serum theophylline concentrations >30 mcg/mL among 6000 blood samples obtained for measurement of serum theophylline concentrations in three emergency departments. Differences in the incidence of manifestations of theophylline toxicity between the two studies may reflect sample selection as a result of study design (e.g., in Study #1, 48% of the patients had acute intoxications versus only 10% in Study #2) and different methods of reporting results.
** NR = Not reported in a comparable manner.

OVERDOSAGE

General:

The chronicity and pattern of theophylline overdosage significantly influences clinical manifestations of toxicity, management and outcome. There are two common presentations: 1) acute overdose, i.e., infusion of an excessive loading dose or excessive maintenance infusion rate for less than 24 hours, and 2) chronic overdosage, i.e., excessive maintenance infusion rate for greater than 24 hours. The most common causes of chronic theophylline overdosage include clinician prescribing of an excessive dose or a normal dose in the presence of factors known to decrease the rate of theophylline clearance and increasing the dose in response to an exacerbation of symptoms without first measuring the serum theophylline concentration to determine whether a dose increase is safe.

Several studies have described the clinical manifestations of theophylline overdose following oral administration and attempted to determine the factors that predict life-threatening toxicity. In general, patients who experience an acute overdose are less likely to experience seizures than patients who have experienced a chronic overdosage, unless the peak serum theophylline concentration is >100 mcg/mL. After a chronic overdosage, generalized seizures, life-threatening cardiac arrhythmias, and death may occur at serum theophylline concentrations >30 mcg/mL. The severity of toxicity after chronic overdosage is more strongly correlated with the patient's age than the peak serum theophylline concentration; patients >60 years are at the greatest risk for severe toxicity and mortality after a chronic overdosage. Pre-existing or concurrent disease may also significantly increase the susceptibility of a patient to a particular toxic manifestation, e.g., patients with neurologic disorders have an increased risk of seizures and patients with cardiac disease have an increased risk of cardiac arrhythmias for a given serum theophylline concentration compared to patients without the underlying disease.

The frequency of various reported manifestations of oral theophylline overdose according to the mode of overdose are listed in Table IV.

Other manifestations of theophylline toxicity include increases in serum calcium, creatine kinase, myoglobin and leukocyte count, decreases in serum phosphate and magnesium, acute myocardial infarction, and urinary retention in men with obstructive uropathy.

Seizures associated with serum theophylline concentrations >30 mcg/mL are often resistant to anticonvulsant therapy and may result in irreversible brain injury if not rapidly controlled. Death from theophylline toxicity is most often secondary to cardiorespiratory arrest and/or hypoxic encephalopathy following prolonged generalized seizures or intractable cardiac arrhythmias causing hemodynamic compromise.

Overdose Management:

General Recommendations for Patients with Symptoms of Theophylline Overdose or Serum Theophylline Concentrations >30 mcg/mL While Receiving Intravenous Theophylline.

1. Stop the theophylline infusion.
2. While simultaneously instituting treatment, contact a regional poison center to obtain updated information and advice on individualizing the recommendations that follow.
3. Institute supportive care, including establishment of intravenous access, maintenance of the airway, and electrocardiographic monitoring.
4. Treatment of seizures:Because of the high morbidity and mortality associated with theophylline-induced seizures, treatment should be rapid and aggressive. Anticonvulsant therapy should be initiated with an intravenous benzodiazepine, e.g., diazepam, in increments of 0.1 - 0.2 mg/kg every 1 - 3 minutes until seizures are terminated. Repetitive seizures should be treated with a loading dose of phenobarbital (20 mg/kg infused over 30 - 60 minutes). Case reports of theophylline overdose in humans and animal studies suggest that phenytoin is ineffective in terminating theophylline-induced seizures. The doses of benzodiazepines and phenobarbital required to terminate theophylline-induced seizures are close to the doses that may cause severe respiratory depression or respiratory arrest; the clinician should therefore be prepared to provide assisted ventilation. Elderly patients and patients with COPD may be more susceptible to the respiratory depressant effects of anticonvulsants. Barbiturate-induced coma or administration of general anesthesia may be required to terminate repetitive seizures or status epilepticus. General anesthesia should be used with caution in patients with theophylline overdose because fluorinated volatile anesthetics may sensitize the myocardium to endogenous catecholamines released by theophylline. Enflurane appears less likely to be associated with this effect than halothane and may, therefore, be safer. Neuromuscular blocking agents alone should not be used to terminate seizures since they abolish the musculoskeletal manifestations without terminating seizure activity in the brain.
5. Anticipate Need for Anticonvulsants:In patients with theophylline overdose who are at high risk for theophylline-induced seizures, e.g., patients with acute overdoses and serum theophylline concentrations >100 mcg/mL or chronic overdosage in patients >60 years of age with serum theophylline concentrations >30 mcg/mL, the need for anticonvulsant therapy should be anticipated. A benzodiazepine such as diazepam should be drawn into a syringe and kept at the patient's bedside and medical personnel qualified to treat seizures should be immediately available. In selected patients at high risk for theophylline-induced seizures, consideration should be given to the administration of prophylactic anticonvulsant therapy. Situations where prophylactic anticonvulsant therapy should be considered in high risk patients include anticipated delays in instituting methods for extracorporeal removal of theophylline (e.g., transfer of a high risk patient from one health care facility to another for extracorporeal removal) and clinical circumstances that significantly interfere with efforts to enhance theophylline clearance (e.g., a neonate where dialysis may not be technically feasible or a patient with vomiting unresponsive to antiemetics who is unable to tolerate multiple-dose oral activated charcoal). In animal studies, prophylactic administration of phenobarbital, but not phenytoin, has been shown to delay the onset of theophylline-induced generalized seizures and to increase the dose of theophylline required to induce seizures (i.e., markedly increases the LD50). Although there are no controlled studies in humans, a loading dose of intravenous phenobarbital (20 mg/kg infused over 60 minutes) may delay or prevent life-threatening seizures in high risk patients while efforts to enhance theophylline clearance are continued. Phenobarbital may cause respiratory depression, particularly in elderly patients and patients with COPD.
6. Treatment of cardiac arrhythmias:Sinus tachycardia and simple ventricular premature beats are not harbingers of life-threatening arrhythmias, they do not require treatment in the absence of hemodynamic compromise, and they resolve with declining serum theophylline concentrations. Other arrhythmias, especially those associated with hemodynamic compromise, should be treated with antiarrhythmic therapy appropriate for the type of arrhythmia.
7. Serum Theophylline Concentration Monitoring:The serum theophylline concentration should be measured immediately upon presentation, 2 - 4 hours later, and then at sufficient intervals, e.g., every 4 hours, to guide treatment decisions and to assess the effectiveness of therapy. Serum theophylline concentrations may continue to increase after presentation of the patient for medical care as a result of continued absorption of theophylline from the gastrointestinal tract. Serial monitoring of serum theophylline serum concentrations should be continued until it is clear that the concentration is no longer rising and has returned to nontoxic levels.
8. General Monitoring Procedures:Electrocardiographic monitoring should be initiated on presentation and continued until the serum theophylline level has returned to a nontoxic level. Serum electrolytes and glucose should be measured on presentation and at appropriate intervals indicated by clinical circumstances. Fluid and electrolyte abnormalities should be promptly corrected. Monitoring and treatment should be continued until the serum concentration decreases below 20 mcg/mL.
9. Enhance clearance of theophylline:Multiple-dose oral activated charcoal (e.g., 0.5 mg/kg up to 20 g, every two hours) increases the clearance of theophylline at least twofold by adsorption of theophylline secreted into gastrointestinal fluids. Charcoal must be retained in, and pass through, the gastrointestinal tract to be effective; emesis should therefore be controlled by administration of appropriate antiemetics. Alternatively, the charcoal can be administered continuously through a nasogastric tube in conjunction with appropriate antiemetics. A single dose of sorbitol may be administered with the activated charcoal to promote stooling to facilitate clearance of the adsorbed theophylline from the gastrointestinal tract. Sorbitol alone does not enhance clearance of theophylline and should be dosed with caution to prevent excessive stooling which can result in severe fluid and electrolyte imbalances. Commercially available fixed combinations of liquid charcoal and sorbitol should be avoided in young children and after the first dose in adolescents and adults since they do not allow for individualization of charcoal and sorbitol dosing. In patients with intractable vomiting, extracorporeal methods of theophylline removal should be instituted (see OVERDOSAGE, Extracorporeal Removal).

Specific Recommendations:

Acute Overdose (e.g., excessive loading dose or excessive infusion rate <24 hours)

1. Serum Concentration >20 <30 mcg/mL
  1. Stop the theophylline infusion.
  2. Monitor the patient and obtain a serum theophylline concentration in 2 - 4 hours to insure that the concentration is decreasing.
2. Serum Concentration >30 <100 mcg/mL
  1. Stop the theophylline infusion.
  2. Administer multiple dose oral activated charcoal and measures to control emesis.
  3. Monitor the patient and obtain serial theophylline concentrations every 2 - 4 hours to gauge the effectiveness of therapy and to guide further treatment decisions.
  4. Institute extracorporeal removal if emesis, seizures, or cardiac arrhythmias cannot be adequately controlled (see OVERDOSAGE, Extracorporeal Removal).
3. Serum Concentration >100 mcg/mL
  1. Stop the theophylline infusion.
  2. Consider prophylactic anticonvulsant therapy.
  3. Administer multiple-dose oral activated charcoal and measures to control emesis.
  4. Consider extracorporeal removal, even if the patient has not experienced a seizure (see OVERDOSAGE, Extracorporeal Removal).
  5. Monitor the patient and obtain serial theophylline concentrations every 2 - 4 hours to gauge the effectiveness of therapy and to guide further treatment decisions.

Chronic Overdosage (e.g., excessive infusion rate for greater than 24 hours)

1. Serum Concentration >20 <30 mcg/mL (with manifestations of theophylline toxicity)
  1. Stop the theophylline infusion.
  2. Monitor the patient and obtain a serum theophylline concentration in 2 - 4 hours to insure that the concentration is decreasing.
2. Serum Concentration >30 mcg/mL in patients <60 years of age
  1. Stop the theophylline infusion.
  2. Administer multiple-dose oral activated charcoal and measures to control emesis.
  3. Monitor the patient and obtain serial theophylline concentrations every 2 - 4 hours to gauge the effectiveness of therapy and to guide further treatment decisions.
  4. Institute extracorporeal removal if emesis, seizures, or cardiac arrhythmias cannot be adequately controlled (see OVERDOSAGE, Extracorporeal Removal).
3. SerumConcentration >30 mcg/mL in patients ≥60 years of age
  1. Stop the theophylline infusion.
  2. Consider prophylactic anticonvulsant therapy.
  3. Administer multiple-dose oral activated charcoal and measures to control emesis.
  4. Consider extracorporeal removal even if the patient has not experienced a seizure (see OVERDOSAGE, Extracorporeal Removal).
  5. Monitor the patient and obtain serial theophylline concentrations every 2 - 4 hours to gauge the effectiveness of therapy and to guide further treatment decisions.

Extracorporeal Removal:

Increasing the rate of theophylline clearance by extracorporeal methods may rapidly decrease serum concentrations, but the risks of the procedure must be weighed against the potential benefit. Charcoal hemoperfusion is the most effective method of extracorporeal removal, increasing theophylline clearance up to six fold, but serious complications, including hypotension, hypocalcemia, platelet consumption and bleeding diatheses may occur. Hemodialysis is about as efficient as multiple-dose oral activated charcoal and has a lower risk of serious complications than charcoal hemoperfusion. Hemodialysis should be considered as an alternative when charcoal hemoperfusion is not feasible and multiple-dose oral charcoal is ineffective because of intractable emesis. Serum theophylline concentrations may rebound 5 - 10 mcg/mL after discontinuation of charcoal hemoperfusion or hemodialysis due to redistribution of theophylline from the tissue compartment. Peritoneal dialysis is ineffective for theophylline removal; exchange transfusions in neonates have been minimally effective.

DOSAGE AND ADMINISTRATION

General Considerations:

The steady-state serum theophylline concentration is a function of the infusion rate and the rate of theophylline clearance in the individual patient. Because of marked individual differences in the rate of theophylline clearance, the dose required to achieve a serum theophylline concentration in the 10-20 mcg/mL range varies fourfold among otherwise similar patients in the absence of factors known to alter theophylline clearance. For a given population there is no single theophylline dose that will provide both safe and effective serum concentrations for all patients. Administration of the median theophylline dose required to achieve a therapeutic serum theophylline concentration in a given population may result in either sub-therapeutic or potentially toxic serum theophylline concentrations in individual patients. The dose of theophylline must be individualized on the basis of serum theophylline concentration measurements in order to achieve a dose that will provide maximum potential benefit with minimal risk of adverse effects.

When theophylline is used as an acute bronchodilator, the goal of obtaining a therapeutic serum concentration is best accomplished with an intravenous loading dose. Because of rapid distribution into body fluids, the serum concentration (C) obtained from an initial loading dose (LD) is related primarily to the volume of distribution (V), the apparent space into which the drug diffuses:

C = LD/V

If a mean volume of distribution of about 0.5 L/kg is assumed (actual range is 0.3 to 0.7 L/kg), each mg/kg (ideal body weight) of theophylline administered as a loading dose over 30 minutes results in an average 2 mcg/mL increase in serum theophylline concentration. Therefore, in a patient who has received no theophylline in the previous 24 hours, a loading dose of intravenous theophylline of 4.6 mg/kg (5.7 mg/kg as aminophylline), calculated on the basis of ideal body weight and administered over 30 minutes, on average, will produce a maximum post-distribution serum concentration of 10 mcg/mL with a range of 6-16 mcg/mL. When a loading dose becomes necessary in the patient who has already received theophylline, estimation of the serum concentration based upon the history is unreliable, and an immediate serum level determination is indicated. The loading dose can then be determined as follows:

D = (Desired C - Measured C) (V)

where D is the loading dose, C is the serum theophylline concentration, and V is the volume of distribution. The mean volume of distribution can be assumed to be 0.5 L/kg and the desired serum concentration should be conservative (e.g., 10 mcg/mL) to allow for the variability in the volume of distribution. A loading dose should not be given before obtaining a serum theophylline concentration if the patient has received any theophylline in the previous 24 hours.

A serum concentration obtained 30 minutes after an intravenous loading dose, when distribution is complete, can be used to assess the need for and size of subsequent loading doses, if clinically indicated, and for guidance of continuing therapy. Once a serum concentration of 10 to 15 mcg/mL has been achieved with the use of a loading dose(s), a constant intravenous infusion is started. The rate of administration is based upon mean pharmacokinetic parameters for the population and calculated to achieve a target serum concentration of 10 mcg/mL (see Table V). For example, in non-smoking adults, initiation of a constant intravenous theophylline infusion of 0.4 mg/kg/hr (0.5 mg/kg/hr as aminophylline) at the completion of the loading dose, on average, will result in a steady-state concentration of 10 mcg/mL with a range of 7-26 mcg/mL. The mean and range of steady-state serum concentrations are similar when the average child (age 1 to 9 years) is given a loading dose of 4.6 mg/kg theophylline (5.7 mg/kg as aminophylline) followed by a constant intravenous infusion of 0.8 mg/kg/hr (1.0 mg/kg/hr as aminophylline). Since there is large interpatient variability in theophylline clearance, serum concentrations will rise or fall when the patient's clearance is significantly different from the mean population value used to calculate the initial infusion rate. Therefore, a second serum concentration should be obtained one expected half-life after starting the constant infusion (e.g., approximately 4 hours for children age 1 to 9 and 8 hours for nonsmoking adults; see Table Ifor the expected half-life in additional patient populations) to determine if the concentration is accumulating or declining from the post loading dose level. If the level is declining as a result of a higher than average clearance, an additional loading dose can be administered and/or the infusion rate increased. In contrast, if the second sample demonstrates a higher level, accumulation of the drug can be assumed, and the infusion rate should be decreased before the concentration exceeds 20 mcg/mL. An additional sample is obtained 12 to 24 hours later to determine if further adjustments are required and then at 24-hour intervals to adjust for changes, if they occur. This empiric method, based upon mean pharmacokinetic parameters, will prevent large fluctuations in serum concentration during the most critical period of the patient's course.

In patients with cor pulmonale, cardiac decompensation, or liver dysfunction, or in those taking drugs that markedly reduce theophylline clearance (e.g., cimetidine), the initial theophylline infusion rate should not exceed 17 mg/hr (21 mg/hr as aminophylline) unless serum concentrations can be monitored at 24-hour intervals. In these patients, 5 days may be required before steady-state is reached.

Theophylline distributes poorly into body fat, therefore, mg/kg dose should be calculated on the basis of ideal body weight.

Table Vcontains initial theophylline infusion rates following an appropriate loading dose recommended for patients in various age groups and clinical circumstances. Table VIcontains recommendations for final theophylline dosage adjustment based upon serum theophylline concentrations. Application of these general dosing recommendations to individual patients must take into account the unique clinical characteristics of each patient. In general, these recommendations should serve as the upper limit for dosage adjustments in order to decrease the risk of potentially serious adverse events associated with unexpected large increases in serum theophylline concentration.

Table V. Initial Theophylline Infusion Rates Following an Appropriate Loading Dose.
Patient population | Age | Theophylline infusion rate (mg/kg/hr)*†
Neonates | Postnatal age up to 24 days; Postnatal age beyond 24 days | 1 mg/kg q12h/‡; 1.5 mg/kg q12h/‡
Infants | 6-52 weeks old | mg/kg/hr= (0.008)(age in weeks) + 0.21
Young children | 1-9 years | 0.8
Older children | 9-12 years | 0.7
Adolescents; (cigarette or marijuana; smokers) | 12-16 years | 0.7
Adolescents (nonsmokers) | 12-16 years | 0.5 §
Adults; (otherwise healthy; nonsmokers) | 16-60 years | 0.4 §
Elderly | >60 years | 0.3 ı
Cardiac decompensation,; cor pulmonale, liver; dysfunction, sepsis with; multiorgan failure,; or shock |  | 0.2 ı
* To achieve a target concentration of 10 mcg/mL Aminophylline=theophylline/0.8. Use ideal body weight for obese patients.
† Lower initial dosage may be required for patients receiving other drugs that decrease theophylline clearance (e.g., cimetidine).
‡ To achieve a target concentration of 7.5 mcg/mL for neonatal apnea.
§ Not to exceed 900 mg/day, unless serum levels indicate the need for a larger dose.
ı Not to exceed 400 mg/day, unless serum levels indicate the need for a larger dose.

Table VI. Final Dosage Adjustment Guided by Serum Theophylline Concentration
Peak Serum Concentration | Dosage Adjustment
<9.9 mcg/mL | If symptoms are not controlled and current dosage is tolerated, increase infusion rate about 25%. Recheck serum concentration after 12 hours in children and 24 hours in adults for further dosage adjustment.
10 to 14.9 mcg/mL | If symptoms are controlled and current dosage is tolerated, maintain infusion rate and recheck serum concentration at 24 hour intervals.¶ If symptoms are not controlled and current dosage is tolerated consider adding additional medication(s) to treatment regimen.
15-19.9 mcg/mL | Consider 10% decrease in infusion rate to provide greater margin of safety even if current dosage is tolerated.¶
20-24.9 mcg/mL | Decrease infusion rate by 25% even if no adverse effects are present. Recheck serum concentration after 12 hours in children and 24 hours in adults to guide further dosage adjustment.
25-30 mcg/mL | Stop infusion for 12 hours in children and 24 hours in adults and decrease subsequent infusion rate at least 25% even if no adverse effects are present. Recheck serum concentration after 12 hours in children and 24 hours in adults to guide further dosage adjustment. If symptomatic, stop infusion and consider whether overdose treatment is indicated (see recommendations for chronic overdosage).
>30 mcg/mL | Stop the infusion and treat overdose as indicated (see recommendations for chronic overdosage). If theophylline is subsequently resumed, decrease infusion rate by at least 50% and recheck serum concentration after 12 hours in children and 24 hours in adults to guide further dosage adjustment.
¶ Dose reduction and/or serum theophylline concentration measurement is indicated whenever adverse effects are present, physiologic abnormalities that can reduce theophylline clearance occur (e.g., sustained fever), or a drug that interacts with theophylline is added or discontinued (see WARNINGS).

Intravenous Admixture Incompatibility:

Although there have been reports of aminophylline precipitating in acidic media, these reports do not apply to the dilute solutions found in intravenous infusions. Aminophylline injection should not be mixed in a syringe with other drugs but should be added separately to the intravenous solution.

When an intravenous solution containing aminophylline is given "piggyback", the intravenous system already in place should be turned off while the aminophylline is infused if there is a potential problem with admixture incompatibility.

Because of the alkalinity of aminophylline containing solutions, drugs known to be alkali labile should be avoided in admixtures. These include epinephrine HCl, norepinephrine bitartrate, isoproterenol HCl and penicillin G potassium. It is suggested that specialized literature be consulted before preparing admixtures with aminophylline and other drugs.

Parenteral drug products should be inspected visually for particulate matter and discoloration prior to administration, whenever solution and container permit. Do not administer unless solution is clear and container is undamaged. Discard unused portion. Do not use if crystals have separated from solution.

HOW SUPPLIED

Aminophylline Injection, USP 25 mg/mL is supplied in single-dose container as follows:

Unit of Sale | Total Strength/Total Volume (Concentration)
NDC 84549-922-01 | 500 mg/20 mL (25 mg/mL)

Store at 20 to 25°C (68 to 77°F). [See USP Controlled Room Temperature.]

PROTECT FROM LIGHT. Store in carton until time of use.

SINGLE-DOSE CONTAINER. Discard unused portion.